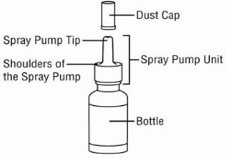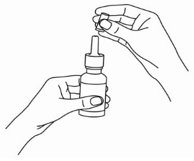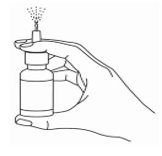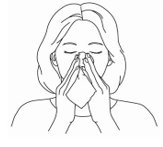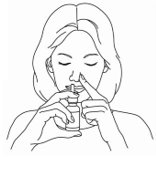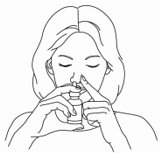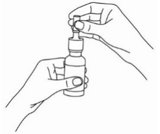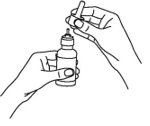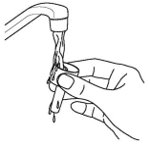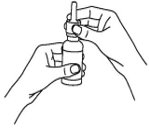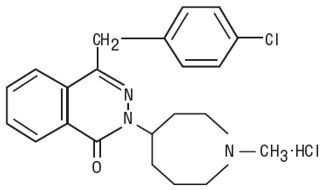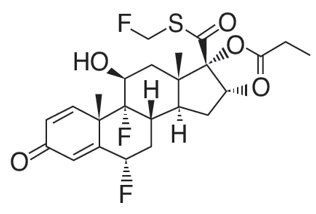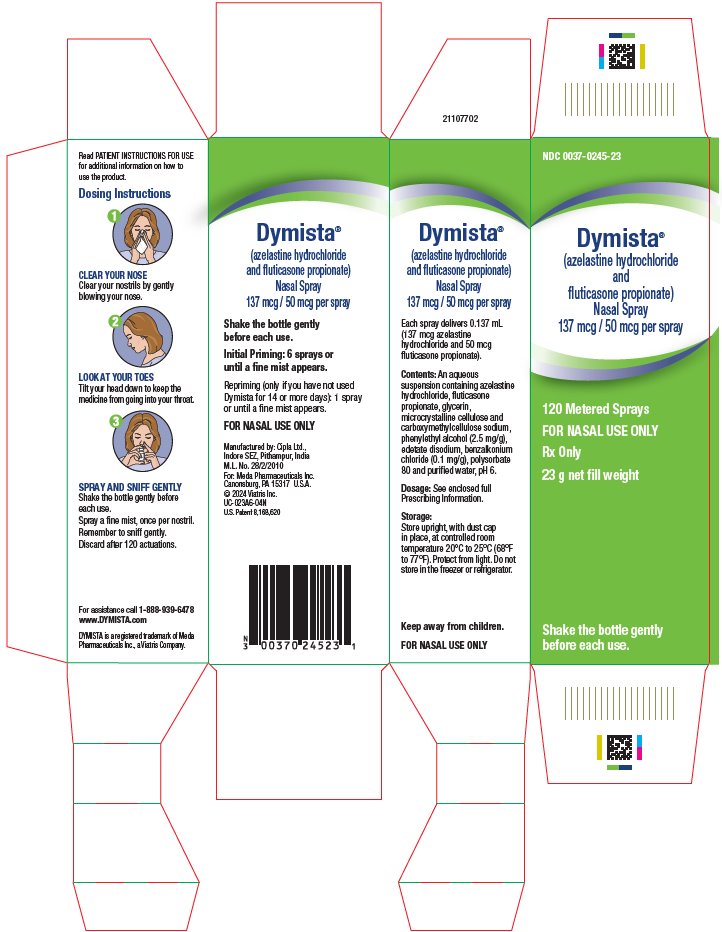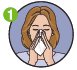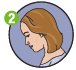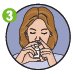 DRUG LABEL: DYMISTA
NDC: 0037-0245 | Form: SPRAY, METERED
Manufacturer: Viatris Specialty LLC
Category: prescription | Type: HUMAN PRESCRIPTION DRUG LABEL
Date: 20241204

ACTIVE INGREDIENTS: AZELASTINE HYDROCHLORIDE 137 ug/1 1; FLUTICASONE PROPIONATE 50 ug/1 1
INACTIVE INGREDIENTS: GLYCERIN; MICROCRYSTALLINE CELLULOSE; CARBOXYMETHYLCELLULOSE SODIUM, UNSPECIFIED; PHENYLETHYL ALCOHOL; EDETATE DISODIUM; BENZALKONIUM CHLORIDE; POLYSORBATE 80; WATER

HIGHLIGHTS OF PRESCRIBING INFORMATION

These highlights do not include all the information needed to use DYMISTA® safely and effectively. See full prescribing information for DYMISTA.
DYMISTA (azelastine hydrochloride and fluticasone propionate) nasal spray
Initial U.S. Approval: 2012

RECENT MAJOR CHANGES

Contraindications (4) 12/2024

1 INDICATIONS AND USAGE

DYMISTA contains an H1-receptor antagonist and a corticosteroid, and is indicated for the relief of symptoms of seasonal allergic rhinitis in adult and pediatric patients 6 years of age and older. (1)

2 DOSAGE AND ADMINISTRATION

- Recommended dosage: 1 spray per nostril twice daily (2.1)
- For nasal use only. (2.2)
- Prime before initial use and when it has not been used for 14 or more days. (2.2)

3 DOSAGE FORMS AND STRENGTHS

Nasal spray: 137 mcg of azelastine hydrochloride and 50 mcg of fluticasone propionate in each spray. (3)

4 CONTRAINDICATIONS

Hypersensitivity to azelastine hydrochloride, fluticasone propionate, or to any ingredients of DYMISTA. Reactions have included anaphylaxis. (4)

5 WARNINGS AND PRECAUTIONS

- Somnolence: Avoid engaging in hazardous occupations requiring complete mental alertness such as driving or operating machinery when taking DYMISTA. (5.1)
- Avoid concurrent use of alcohol or other central nervous system (CNS) depressants with DYMISTA because further decreased alertness and impairment of CNS performance may occur. (5.1)
- Epistaxis, nasal ulcerations, nasal septal perforation, impaired wound healing, Candida albicans infection: Monitor patients periodically for signs of adverse effects on the nasal mucosa. Avoid use in patients with recent nasal ulcers, nasal surgery, or nasal trauma. (5.2)
- Glaucoma or posterior subcapsular cataracts: Monitor patients closely with a change in vision or with a history of increased intraocular pressure, glaucoma, and/or cataracts. (5.3)
- Potential worsening of existing tuberculosis; fungal, bacterial, viral, or parasitic infections; or ocular herpes simplex. More serious or even fatal course of chickenpox or measles in susceptible patients. Use caution in patients with the above because of the potential for worsening of these infections. (5.4)
- Hypercorticism and adrenal suppression with very high dosages or at the regular dosage in susceptible individuals. If such changes occur, discontinue DYMISTA slowly. (5.5)
- Potential reduction in growth velocity in children. Monitor growth routinely in pediatric patients receiving DYMISTA. (5.7, 8.4)

6 ADVERSE REACTIONS

The most common adverse reactions (≥2% incidence) are: dysgeusia, epistaxis, and headache. (6.1)

To report SUSPECTED ADVERSE REACTIONS, contact Meda Pharmaceuticals Inc. at 1-888-939-6478 or FDA at 1-800-FDA-1088 or www.fda.gov/medwatch.

7 DRUG INTERACTIONS

- Potent inhibitors of cytochrome P450 (CYP) 3A4: May increase blood levels of fluticasone propionate.
- Ritonavir: Coadministration is not recommended. (5.6, 7.2)
- Other potent CYP3A4 inhibitors, such as ketoconazole: use caution with coadministration. (5.6, 7.2)

FULL PRESCRIBING INFORMATION

1 INDICATIONS AND USAGE

DYMISTA is indicated for the relief of symptoms of seasonal allergic rhinitis in adult and pediatric patients 6 years of age and older.

2 DOSAGE AND ADMINISTRATION

2.1 Recommended Dosage

The recommended dosage of DYMISTA is 1 spray (137 mcg of azelastine hydrochloride and 50 mcg of fluticasone propionate) in each nostril twice daily.

2.2 Important Administration Instructions

- Administer DYMISTA by the nasal route only.
- Shake the bottle gently before each use.
- Avoid spraying DYMISTA into the eyes. If sprayed in the eyes, flush eyes with water for at least 10 minutes.

Priming

Prime DYMISTA before initial use by releasing 6 sprays or until a fine mist appears.

Repriming (as needed)

When DYMISTA has not been used for 14 or more days, reprime with 1 spray or until a fine mist appears.

3 DOSAGE FORMS AND STRENGTHS

Nasal spray: 137 mcg of azelastine hydrochloride and 50 mcg of fluticasone propionate per spray.

4 CONTRAINDICATIONS

DYMISTA is contraindicated in patients with hypersensitivity to azelastine hydrochloride, fluticasone propionate, or to any other ingredients of DYMISTA. Reactions have included anaphylaxis [see Adverse Reactions (6.2)].

5 WARNINGS AND PRECAUTIONS

5.1 Somnolence

In clinical trials, the occurrence of somnolence has been reported in some patients (6 of 853 adult and adolescent patients and 2 of 416 children) taking DYMISTA in placebo controlled trials [see Adverse Reactions (6.1)]. Patients should be cautioned against engaging in hazardous occupations requiring complete mental alertness and motor coordination such as operating machinery or driving a motor vehicle after administration of DYMISTA. Concurrent use of DYMISTA with alcohol or other central nervous system depressants should be avoided because additional reductions in alertness and additional impairment of central nervous system performance may occur [see Drug Interactions (7.1)].

5.2 Local Nasal Effects

In clinical trials of 2 to 52 weeks’ duration, epistaxis was observed more frequently in patients treated with DYMISTA than those who received placebo [see Adverse Reactions (6)].

Instances of nasal ulceration and nasal septal perforation have been reported in patients following the nasal application of corticosteroids. There were no instances of nasal ulceration or nasal septal perforation observed in clinical trials with DYMISTA.

Because of the inhibitory effect of corticosteroids on wound healing, patients who have experienced recent nasal ulcers, nasal surgery, or nasal trauma should avoid use of DYMISTA until healing has occurred.

In clinical trials with fluticasone propionate administered nasally, the development of localized infections of the nose and pharynx with Candida albicans has occurred. When such an infection develops, it may require treatment with appropriate local therapy and discontinuation of treatment with DYMISTA. Patients using DYMISTA over several months or longer should be examined periodically for evidence of Candida infection or other signs of adverse effects on the nasal mucosa.

5.3 Glaucoma and Cataracts

Nasal and inhaled corticosteroids may result in the development of glaucoma and/or cataracts. Therefore, close monitoring is warranted in patients with a change in vision or with a history of increased intraocular pressure, glaucoma, and/or cataracts.

Glaucoma and cataract formation were evaluated with intraocular pressure measurements and slit lamp examinations in a controlled 12-month study in 612 adolescent and adult patients aged 12 years and older with perennial allergic or vasomotor rhinitis (VMR). Of the 612 patients enrolled in the study, 405 were randomized to receive DYMISTA (1 spray per nostril twice daily) and 207 were randomized to receive fluticasone propionate nasal spray (2 sprays per nostril once daily). In the DYMISTA group, one patient had increased intraocular pressure at month 6. In addition, three patients had evidence of posterior subcapsular cataract at month 6 and one at month 12 (end of treatment). In the fluticasone propionate group, three patients had evidence of posterior subcapsular cataract at month 12 (end of treatment).

5.4 Immunosuppression and Risk of Infections

Persons who are using drugs, such as corticosteroids, that suppress the immune system are more susceptible to infections than healthy individuals. Chickenpox and measles, for example, can have a more serious or even fatal course in susceptible children or adults using corticosteroids. In children or adults who have not had these diseases or been properly immunized, particular care should be taken to avoid exposure. How the dose, route, and duration of corticosteroid administration affect the risk of developing a disseminated infection is not known. The contribution of the underlying disease and/or prior corticosteroid treatment to the risk is also not known. If exposed to chickenpox, prophylaxis with varicella zoster immune globulin (VZIG) may be indicated. If exposed to measles, prophylaxis with pooled intramuscular immunoglobulin (IG) may be indicated. (See the respective Prescribing Information for VZIG and IG.) If chickenpox develops, treatment with antiviral agents may be considered.

Corticosteroids should be used with caution, if at all, in patients with active or quiescent tuberculous infections of the respiratory tract; untreated local or systemic fungal or bacterial infections; systemic viral or parasitic infections; or ocular herpes simplex because of the potential for worsening of these infections.

5.5 Hypercorticism and Adrenal Suppression

When nasal steroids are used at higher than recommended dosages or in susceptible individuals at recommended dosages, systemic corticosteroid effects such as hypercorticism and adrenal suppression may appear. If such changes occur, the dosage of DYMISTA should be discontinued slowly, consistent with accepted procedures for discontinuing oral corticosteroid therapy. The concomitant use of nasal corticosteroids with other inhaled corticosteroids could increase the risk of signs or symptoms of hypercorticism and/or suppression of the HPA axis.

The replacement of a systemic corticosteroid with a topical corticosteroid can be accompanied by signs of adrenal insufficiency, and in addition some patients may experience symptoms of withdrawal, e.g., joint and/or muscular pain, lassitude, and depression. Patients previously treated for prolonged periods with systemic corticosteroids and transferred to topical corticosteroids should be carefully monitored for acute adrenal insufficiency in response to stress. In those patients who have asthma or other clinical conditions requiring long-term systemic corticosteroid treatment, too rapid a decrease in systemic corticosteroids may cause a severe exacerbation of their symptoms.

5.6 Use of Cytochrome P450 3A4 Inhibitors

Ritonavir and other strong cytochrome P450 3A4 (CYP3A4) inhibitors can significantly increase plasma fluticasone propionate exposure, resulting in significantly reduced serum cortisol concentrations [see Drug Interactions (7.2) and Clinical Pharmacology (12.3)]. During postmarketing use, there have been reports of clinically significant drug interactions in patients receiving fluticasone propionate and ritonavir, resulting in systemic corticosteroid effects including Cushing syndrome and adrenal suppression. Therefore, coadministration of DYMISTA and ritonavir is not recommended unless the potential benefit to the patient outweighs the risk of systemic corticosteroid side effects.

Use caution with the coadministration of DYMISTA and other potent CYP3A4 inhibitors, such as ketoconazole [see Drug Interactions (7.2) and Clinical Pharmacology (12.3)].

5.7 Effect on Growth

Corticosteroids may cause a reduction in growth velocity when administered to pediatric patients. Monitor the growth routinely of pediatric patients receiving DYMISTA [see Use in Specific Populations (8.4)].

6 ADVERSE REACTIONS

The following clinically significant adverse reactions are described elsewhere in the labeling:

- Somnolence [see Warnings and Precautions (5.1)]
- Local nasal effects, including epistaxis, nasal ulceration, nasal septal perforation, impaired wound healing, and Candida albicans infection [see Warnings and Precautions (5.2)]
- Glaucoma and Cataracts [see Warnings and Precautions (5.3)]
- Immunosuppression and Risk of Infections [see Warnings and Precautions (5.4)]
- Hypercorticism and Adrenal Suppression, including growth reduction [see Warnings and Precautions (5.5 and 5.7), Use in Specific Populations (8.4)]

6.1 Clinical Trials Experience

Because clinical trials are conducted under widely varying conditions, adverse reaction rates observed in clinical trials of a drug cannot be directly compared to rates in the clinical trials of another drug and may not reflect rates observed in practice.

Adults and Adolescents 12 Years of Age and Older

The safety data described below in adults and adolescents 12 years of age and older reflect exposure to DYMISTA in 853 patients (12 years of age and older; 36% male and 64% female) with seasonal allergic rhinitis in 3 double-blind, placebo-controlled clinical trials of 2-week duration. The racial distribution for the 3 clinical trials was 80% white, 16% black, 2% Asian, and 1% other.

In the 3 placebo controlled clinical trials of 2-week duration, 3411 patients with seasonal allergic rhinitis were treated with 1 spray per nostril of DYMISTA, azelastine hydrochloride nasal spray, fluticasone propionate nasal spray, or placebo, twice daily. The azelastine hydrochloride and fluticasone propionate comparators use the same vehicle and device as DYMISTA and are not commercially marketed. Overall, adverse reactions were 16% in the DYMISTA treatment groups, 15% in the azelastine hydrochloride nasal spray groups, 13% in the fluticasone propionate nasal spray groups, and 12% in the placebo groups. Overall, 1% of patients in both the DYMISTA and placebo groups discontinued due to adverse reactions.

Table 1 contains adverse reactions reported with frequencies greater than or equal to 2% and more frequently than placebo in patients treated with DYMISTA in the seasonal allergic rhinitis controlled clinical trials.

Table 1. Adverse Reactions with ≥ 2% Incidence and More Frequently than Placebo in Placebo-Controlled Trials of 2 Weeks Duration with DYMISTA in Adult and Adolescent Patients with Seasonal Allergic Rhinitis
 | 1 spray per nostril twice daily
 | DYMISTA; (N = 853) [Safety population N = 853, intent-to-treat population N = 848] | Azelastine Hydrochloride Nasal Spray [Not commercially marketed]; (N = 851) | Fluticasone Propionate Nasal Spray; (N = 846) | Vehicle Placebo; (N = 861)
Dysgeusia | 30 (4%) | 44 (5%) | 4 (1%) | 2 (< 1%)
Headache | 18 (2%) | 20 (2%) | 20 (2%) | 10 (1%)
Epistaxis | 16 (2%) | 14 (2%) | 14 (2%) | 15 (2%)

In the above trials, somnolence was reported in < 1% of patients treated with DYMISTA (6 of 853) or vehicle placebo (1 of 861) [see Warnings and Precautions (5.1)].

Pediatric Patients 6-11 Years of Age

The safety data described below in children 6-11 years of age reflect exposure to DYMISTA in 152 patients (6-11 years of age; 57% male and 43% female) with seasonal allergic rhinitis in one double-blind, placebo-controlled clinical trial of 2-week duration. The racial distribution for the clinical trial was 69% white, 31% black, 2% Asian and 2% other.

In the placebo-controlled clinical trial of 2-week duration, patients with seasonal allergic rhinitis were treated with 1 spray per nostril of DYMISTA or placebo, twice daily. Overall, adverse reactions were 16% in the DYMISTA treatment group, and 12% in the placebo group. Overall, 1% of patients in both the DYMISTA and placebo groups discontinued due to adverse reactions.

Table 2 contains adverse reactions reported with frequencies greater than or equal to 2% and more frequently than placebo in patients treated with DYMISTA in the seasonal allergic rhinitis controlled clinical trial.

Table 2. Adverse Reactions with ≥ 2% Incidence and More Frequently than Placebo in Placebo-Controlled Trials of 2 Weeks Duration with DYMISTA in Children 6 to 11 Years of Age with Seasonal Allergic Rhinitis
 | 1 spray per nostril twice daily
 | DYMISTA; (N = 152) [Safety population N = 152, intent-to-treat population N = 152] | Vehicle Placebo; (N = 152)
Dysgeusia | 6 (4%) | 0 (0%)
Epistaxis | 6 (4%) | 4 (3%)

In the above trial, somnolence was not reported [see Warnings and Precautions (5.1)].

Long-Term (12-Month) Safety Trial in Adults and Adolescents 12 Years of Age and Older

In the 12-month open-label, active-controlled clinical trial, 404 Asian patients (240 males and 164 females) with perennial allergic rhinitis or vasomotor rhinitis were treated with DYMISTA, 1 spray per nostril twice daily.

In the 12-month, open-label, active-controlled, long-term safety trial in adults and adolescents 12 years of age and older, 404 patients with perennial allergic rhinitis or vasomotor rhinitis were treated with DYMISTA 1 spray per nostril twice daily and 207 patients were treated with fluticasone propionate nasal spray, 2 sprays per nostril once daily. Overall, adverse reactions were 47% in the DYMISTA treatment group and 44% in the fluticasone propionate nasal spray group. The most frequently reported adverse reactions (≥ 2%) with DYMISTA were headache, pyrexia, cough, nasal congestion, rhinitis, dysgeusia, viral infection, upper respiratory tract infection, pharyngitis, pain, diarrhea, and epistaxis. In the DYMISTA treatment group, 7 patients (2%) had mild epistaxis and 1 patient (< 1%) had moderate epistaxis. In the fluticasone propionate nasal spray treatment group 1 patient (< 1%) had mild epistaxis. No patients had reports of severe epistaxis. Focused nasal examinations were performed and no nasal ulcerations or septal perforations were observed. Eleven of 404 patients (3%) treated with DYMISTA and 6 of 207 patients (3%) treated with fluticasone propionate nasal spray discontinued from the trial due to adverse reactions.

Long-Term (3-Month) Safety Trial in Pediatric Patients 6-11 Years of Age

In the 3-month open label active-controlled clinical trial, 264 patients (60% male, 40% female) (80% white, 19% black, 4% Asian and 2% other) with allergic rhinitis were treated with DYMISTA, 1 spray per nostril twice daily.

In the 3-month, open label, active-controlled, safety trial in pediatric patients 6-11 years of age 264 patients (128 patients ≥ 6 to < 9 years of age, and 136 patients ≥ 9 to < 12 years of age) with allergic rhinitis (based on the Investigator’s assessment) were treated with DYMISTA, 1 spray per nostril twice daily and 89 patients (44 patients ≥ 6 to < 9 years of age, and 45 patients ≥ 9 to < 12 years of age) were treated with fluticasone propionate nasal spray, 1 spray per nostril twice daily. Overall, adverse reactions were 40% in the DYMISTA treatment group and 36% in the fluticasone propionate nasal spray group. The most frequently reported adverse reactions (≥ 2%) with DYMISTA were epistaxis, headache, oropharyngeal pain, vomiting, upper abdominal pain, cough, pyrexia, otitis media, upper respiratory tract infection, diarrhea, nausea, otitis externa, and urticaria. In the DYMISTA treatment group 23 patients (9%) had mild epistaxis and 3 patients (1%) had moderate epistaxis. In the fluticasone propionate nasal spray treatment group 8 patients (9%) had mild epistaxis. No patients had reports of severe epistaxis. Focused nasal examinations were performed and no ulcerations or septal perforations were observed. Four of 264 patients (2%) treated with DYMISTA and 3 of 89 (3%) treated with fluticasone propionate nasal spray discontinued from the trial due to adverse reactions. There were two reports of somnolence, one severe, among children taking DYMISTA [see Warnings and Precautions (5.1)].

6.2 Postmarketing Experience

The following spontaneous adverse reactions have been reported with DYMISTA or one of the components (azelastine and fluticasone). Because these reactions are reported voluntarily from a population of uncertain size, it is not always possible to reliably estimate their frequency or establish a causal relationship to drug exposure.

Cardiac Disorders: atrial fibrillation, increased heart rate, palpitations

Eye Disorder: blurred vision, cataracts, conjunctivitis, dryness and irritation, eye swelling, glaucoma, increased intraocular pressure, vision abnormal, xerophthalmia

Gastrointestinal Disorders: nausea, vomiting

General Disorders and Administration Site Condition: aches and pain, application site irritation, chest pain, edema of face and tongue, fatigue, tolerance

Immune System Disorders: anaphylaxis

Musculoskeletal and Connective Tissue Disorders: growth suppression [see Use in Specific Populations (8.4)]

Nervous System Disorders: disturbance or loss of smell and/or taste, dizziness, involuntary muscle contractions, paresthesia, parosmia

Psychiatric Disorders: anxiety, confusion, nervousness

Renal and Urinary Disorders: urinary retention

Respiratory, Thoracic and Mediastinal Disorders: bronchospasm, cough, dysphonia, dyspnea, hoarseness, nasal septal perforation, nasal discomfort, nasal dryness, nasal sores, nasal ulcer, sore throat, throat dryness and irritation, voice changes, wheezing

Skin and Subcutaneous Tissue Disorder: angioedema, erythema, face swelling, pruritus, rash, urticaria

Vascular Disorder: hypertension

7 DRUG INTERACTIONS

No formal drug interaction studies have been performed with DYMISTA. The drug interactions of the combination are expected to reflect those of the individual components.

7.1 Central Nervous System Depressants

Concurrent use of DYMISTA with alcohol or other central nervous system depressants should be avoided because somnolence and impairment of central nervous system performance may occur [see Warnings and Precautions (5.1)].

7.2 Cytochrome P450 3A4

Ritonavir (a strong CYP3A4 inhibitor) significantly increased plasma fluticasone propionate exposure following administration of fluticasone propionate aqueous nasal spray, resulting in significantly reduced serum cortisol concentrations [see Clinical Pharmacology (12.3)]. During postmarketing use, there have been reports of clinically significant drug interactions in patients receiving fluticasone propionate and ritonavir, resulting in systemic corticosteroid effects including Cushing syndrome and adrenal suppression. Therefore, coadministration of fluticasone propionate and ritonavir is not recommended unless the potential benefit to the patient outweighs the risk of systemic corticosteroid side effects.

Ketoconazole (also a strong CYP3A4 inhibitor), administered in multiple 200 mg doses to steady-state, increased plasma exposure of fluticasone propionate, reduced plasma cortisol AUC, but had no effect on urinary excretion of cortisol, following administration of a single 1000 mcg dose of fluticasone propionate by oral inhalation route.

Caution should be exercised when DYMISTA is coadministered with ketoconazole and other known strong CYP3A4 inhibitors.

8 USE IN SPECIFIC POPULATIONS

8.1 Pregnancy

Risk Summary

Limited data from postmarketing experience with DYMISTA in pregnant women have not identified any drug associated risks of miscarriage, birth defects, or other adverse maternal or fetal outcomes. The individual components of DYMISTA have been marketed for decades. While the data regarding the use of nasal preparations of fluticasone propionate in pregnancy are limited, data from clinical studies of inhaled fluticasone propionate do not indicate an increased risk of adverse maternal or fetal outcomes.

Animal reproduction studies with DYMISTA are not available; however, studies are available with its individual components, azelastine hydrochloride and fluticasone propionate. In animal reproduction studies, there was no evidence of fetal harm in animals at oral doses of azelastine hydrochloride approximately 10 times the clinical daily dose. Oral administration of azelastine hydrochloride to pregnant mice, rats, and rabbits, during the period of organogenesis, produced developmental toxicity that included structural abnormalities, decreased embryo-fetal survival, and decreased fetal body weights at doses 530 times and higher than the maximum recommended human daily nasal dose (MRHDID) of 0.548 mg. However, the relevance of these findings in animals to pregnant women was considered questionable based upon the high animal to human dose multiple.

In animal reproduction studies, fluticasone propionate administered via nose-only inhalation to rats decreased fetal body weight, but did not induce teratogenicity at a maternal toxic dose less than the MRHDID on a mcg/m^2 basis. Teratogenicity, characteristic of corticosteroids, decreased fetal body weight and/or skeletal variations, in rats, mice, and rabbits were observed with subcutaneously administered maternal toxic doses of fluticasone propionate less than the MRHDID of 200 mcg on a mcg/m^2 basis (see Data). Experience with corticosteroids suggests that rodents are more prone to teratogenic effects from corticosteroids than humans.

The estimated background risk of major birth defects and miscarriage for the indicated populations is unknown. All pregnancies have a background risk of birth defect, loss, or other adverse outcomes. In the U.S. general population, the estimated background risk of major birth defects and miscarriage in clinically recognized pregnancies is 2-4% and 15-20%, respectively.

Data

Animal Data

Azelastine Hydrochloride: In an embryo-fetal development study in mice dosed during the period of organogenesis, azelastine hydrochloride caused embryo-fetal death, structural abnormalities (cleft palate; short or absent tail; fused, absent or branched ribs), delayed ossification, and decreased fetal weight at approximately 610 times the MRHDID in adults (on a mg/m^2 basis at a maternal oral dose of 68.6 mg/kg/day), which also caused maternal toxicity as evidenced by decreased maternal body weight. Neither fetal nor maternal effects occurred in mice at approximately 25 times the MRHDID in adults (on a mg/m^2 basis at a maternal oral dose of 3 mg/kg/day).

In an embryo-fetal development study in pregnant rats dosed during the period of organogenesis from gestation days 7 to 17, azelastine hydrochloride caused structural abnormalities (oligo- and brachydactylia), delayed ossification, and skeletal variations, in the absence of maternal toxicity, at approximately 530 times the MRHDID in adults (on a mg/m^2 basis at a maternal oral dose of 30 mg/kg/day). Azelastine hydrochloride caused embryo-fetal death and decreased fetal weight and severe maternal toxicity at approximately 1200 times the MRHDID (on a mg/m^2 basis at a maternal oral dose of 68.6 mg/kg/day). Neither fetal nor maternal effects occurred at approximately 55 times the MRHDID (on a mg/m^2 basis at a maternal oral dose of 3 mg/kg/day).

In an embryo-fetal development study in pregnant rabbits dosed during the period of organogenesis from gestation days 6 to 18, azelastine hydrochloride caused abortion, delayed ossification and decreased fetal weight and severe maternal toxicity at approximately 1100 times the MRHDID in adults (on a mg/m^2 basis at a maternal oral dose of 30 mg/kg/day). Neither fetal nor maternal effects occurred at approximately 10 times the MRHDID (on a mg/m^2 basis at a maternal oral dose of 0.3 mg/kg/day).

In a prenatal and postnatal development study in pregnant rats dosed from late in the gestation period and through the lactation period from gestation day 17 through lactation day 21, azelastine hydrochloride produced no adverse developmental effects on pups at maternal doses up to approximately 530 times the MRHDID (on mg/m^2 basis at a maternal dose of 30 mg/kg/day).

Fluticasone Propionate: In embryofetal development studies with pregnant rats and mice dosed by the subcutaneous route throughout the period of organogenesis, fluticasone propionate was teratogenic in both species. Omphalocele, decreased body weight, and skeletal variations were observed in rat fetuses, in the presence of maternal toxicity, at a dose approximately 5 times the MRHDID (on a mg/m^2 basis with a maternal subcutaneous dose of 100 mcg/kg/day). Neither fetal nor maternal effects occurred in rats at approximately 1 times the MRHDID (on a mg/m^2 basis with a maternal subcutaneous dose of 30 mcg/kg/day). Cleft palate and fetal skeletal variations were observed in mouse fetuses at a dose approximately 1 times the MRHDID (on a mg/m^2 basis with a maternal subcutaneous dose of 45 mcg/kg/day). Neither fetal nor maternal effects occurred in mice with a dose approximately 0.4 times the MRHDID (on a mg/m^2 basis with a maternal subcutaneous dose of 15 mcg/kg/day).

In an embryofetal development study with pregnant rats dosed by the nose-only inhalation route throughout the period of organogenesis, fluticasone propionate produced decreased fetal body weights and skeletal variations, in the presence of maternal toxicity, at a dose approximately 1 times the MRHDID (on a mg/m^2 basis with a maternal nose-only inhalation dose of 25.7 mcg/kg/day); however, there was no evidence of teratogenicity. Neither fetal nor maternal effects occurred in rats with a dose approximately 0.25 times the MRHDID (on a mg/m^2 basis with a maternal nose-only inhalation dose of 5.5 mcg/kg/day).

In an embryofetal development study in pregnant rabbits that were dosed by the subcutaneous route throughout organogenesis, fluticasone propionate produced reductions of fetal body weights, in the presence of maternal toxicity, at doses approximately 0.06 times the MRHDID and higher (on a mg/m^2 basis with a maternal subcutaneous dose of 0.57 mcg/kg/day). Teratogenicity was evident based upon a finding of cleft palate for 1 fetus at dose approximately 0.4 times the MRHDID (on a mg/m^2 basis with a maternal subcutaneous dose of 4 mcg/kg/day). Neither fetal nor maternal effects occurred in rabbits with a dose approximately 0.01 times the MRHDID (on a mg/m^2 basis with a maternal subcutaneous dose of 0.08 mcg/kg/day).

Fluticasone propionate crossed the placenta following subcutaneous administration to mice and rats and oral administration to rabbits.

In a pre- and post-natal development study in pregnant rats dosed from late gestation through delivery and lactation (Gestation Day 17 to Postpartum Day 22), fluticasone propionate was not associated with decreases in pup body weight, and had no effects on developmental landmarks, learning, memory, reflexes, or fertility at doses up to 2 times the MRHDID (on a mg/m^2 basis with maternal subcutaneous doses up to 50 mcg/kg/day).

8.2 Lactation

Risk Summary

There are no available data on the presence of azelastine hydrochloride or fluticasone propionate in human milk, the effects on the breastfed infant, or the effects on milk production. Breastfed infants should be monitored for signs of milk rejection during DYMISTA use by lactating women (see Clinical Considerations). Fluticasone propionate is present in rat milk (see Data). Other corticosteroids have been detected in human milk. However, fluticasone propionate concentrations in plasma after nasal therapeutic doses are low and therefore concentrations in human breast milk are likely to be correspondingly low [see Clinical Pharmacology (12.3)]. The developmental and health benefits of breastfeeding should be considered along with the mother’s clinical need for DYMISTA and any potential adverse effects on the breastfed infant from DYMISTA or from the underlying maternal condition.

Clinical Considerations

Monitoring for Adverse Reactions

Breastfed infants of lactating women treated with DYMISTA should be monitored for possible signs of milk rejection related to the bitter taste of azelastine hydrochloride.

Data

Subcutaneous administration of 10 mcg/kg of tritiated fluticasone propionate to lactating rats resulted in measurable radioactivity in the milk.

8.4 Pediatric Use

The safety and effectiveness of DYMISTA for seasonal allergic rhinitis have been established in pediatric patients aged 6 years and older. Use of DYMISTA for this indication in pediatric patients 6 to 11 years of age is supported by evidence from controlled clinical trials (416 patients 6 to 11 years of age with allergic rhinitis were treated with DYMISTA) [see Adverse Reactions (6.1) and Clinical Studies (14)].

Sixty-one patients ages 4-5 years of age were treated with DYMISTA in the pediatric studies described above. Safety findings in children 4-5 years of age were similar to those in children 6-11 years of age, but effectiveness has not been established.

Safety and effectiveness of DYMISTA have not been established in pediatric patients below the age of 4 years.

Controlled clinical studies have shown that nasal corticosteroids may cause a reduction in growth velocity in pediatric patients. This effect has been observed in the absence of laboratory evidence of HPA axis suppression, suggesting that growth velocity is a more sensitive indicator of systemic corticosteroid exposure in pediatric patients than some commonly used tests of HPA axis function. The long-term effects of this reduction in growth velocity associated with nasal corticosteroids, including the impact on final adult height, are unknown. The potential for “catch-up” growth following discontinuation of treatment with nasal corticosteroids has not been adequately studied. The growth of pediatric patients receiving nasal corticosteroids, including DYMISTA, should be monitored routinely (e.g., via stadiometry). The potential growth effects of prolonged treatment should be weighed against the clinical benefits obtained and the risks/benefits of treatment alternatives.

8.5 Geriatric Use

Clinical trials of DYMISTA did not include sufficient numbers of patients 65 years of age and older to determine whether they respond differently from younger patients. Other reported clinical experience has not identified differences in responses between the elderly and younger patients. In general, dose selection for an elderly patient should be cautious, usually starting at the low end of the dosing range, reflecting the greater frequency of decreased hepatic, renal, or cardiac function, and of concomitant disease or other drug therapy.

10 OVERDOSAGE

DYMISTA: DYMISTA contains both azelastine hydrochloride and fluticasone propionate; therefore, the risks associated with overdosage for the individual components described below apply to DYMISTA.

Azelastine Hydrochloride: There have been no reported overdosages with azelastine hydrochloride. Acute azelastine hydrochloride overdosage by adults with this dosage form is unlikely to result in clinically significant adverse reactions, other than increased somnolence, since one (1) 23 g bottle of DYMISTA contains approximately 23 mg of azelastine hydrochloride. General supportive measures should be employed if overdosage occurs. There is no known antidote to DYMISTA. Oral ingestion of antihistamines has the potential to cause serious adverse effects in children. Accordingly, DYMISTA should be kept out of the reach of children.

Fluticasone Propionate: Chronic fluticasone propionate overdosage may result in signs/symptoms of hypercorticism [see Warnings and Precautions (5.5)].

11 DESCRIPTION

DYMISTA (azelastine hydrochloride and fluticasone propionate) nasal spray is formulated as a white, uniform metered-spray suspension for nasal administration. It is a fixed dose combination product containing an antihistamine (H1 receptor antagonist) and a corticosteroid as active ingredients.

Azelastine hydrochloride active ingredient occurs as a white, odorless, crystalline powder with a bitter taste. It has a molecular weight of 418.37. It is sparingly soluble in water, methanol, and propylene glycol and slightly soluble in ethanol, octanol, and glycerin. It has a melting point of 225°C and the pH of 5.2. Its chemical name is (±)-1-(2H)-phthalazinone,4-[(4-chlorophenyl) methyl]-2-(hexahydro-1-methyl-1H-azepin-4-yl)-, monohydrochloride. Its molecular formula is C22H24ClN3O•HCl with the following chemical structure:

Fluticasone propionate active ingredient is a white powder with a melting point of 273°C, a molecular weight of 500.6, and the empirical formula is C25H31F3O5S. It is practically insoluble in water, freely soluble in dimethyl sulfoxide and dimethylformamide, and slightly soluble in methanol and 95% ethanol. Fluticasone propionate is a synthetic corticosteroid having the chemical name S-(fluoromethyl)-6α,9α-difluoro-11β-17-dihydroxy-16α-methyl-3-oxoandrosta-1,4-diene-17β-carbothioate, 17-propionate, and the following chemical structure:

DYMISTA (azelastine hydrochloride and fluticasone propionate) nasal spray, 137 mcg/50 mcg contains 0.1% solution of azelastine hydrochloride and 0.037% suspension of micronized fluticasone propionate in an isotonic aqueous suspension containing benzalkonium chloride (0.1 mg/g), carboxymethylcellulose sodium, edetate disodium, glycerin, microcrystalline cellulose, phenylethyl alcohol (2.5 mg/g), polysorbate 80, and purified water. It has a pH of approximately 6.0.

After priming [see Dosage and Administration (2.2)], each metered spray delivers a 0.137 mL mean volume of suspension containing 137 mcg of azelastine hydrochloride (equivalent to 125 mcg of azelastine base) and 50 mcg of fluticasone propionate. The 23 g bottle provides 120 metered sprays, after priming.

12 CLINICAL PHARMACOLOGY

12.1 Mechanism of Action

DYMISTA

DYMISTA contains both azelastine hydrochloride and fluticasone propionate; therefore, the mechanisms of actions described below for the individual components apply to DYMISTA. These drugs represent two different classes of medications (histamine H1-receptor antagonist and synthetic corticosteroid).

Azelastine Hydrochloride

Azelastine hydrochloride, a phthalazinone derivative, exhibits histamine H1-receptor antagonist activity in isolated tissues, animal models, and humans. Azelastine hydrochloride in DYMISTA is administered as a racemic mixture with no difference in pharmacologic activity noted between the enantiomers in in vitro studies. The major metabolite, desmethylazelastine, also possesses H1-receptor antagonist activity.

Fluticasone Propionate

Fluticasone propionate is a synthetic trifluorinated corticosteroid with anti-inflammatory activity. In vitro dose response studies on a cloned human glucocorticoid receptor system involving binding and gene expression afforded 50% responses at 1.25 and 0.17 nM concentrations, respectively. Fluticasone propionate was 3-fold to 5-fold more potent than dexamethasone in these assays. Data from the McKenzie vasoconstrictor assay in man also support its potent glucocorticoid activity. The clinical relevance of these findings is unknown.

The precise mechanism through which fluticasone propionate affects allergic rhinitis symptoms is not known. Corticosteroids have been shown to have a wide range of effects on multiple cell types (e.g., mast cells, eosinophils, neutrophils, macrophages, and lymphocytes) and mediators (e.g., histamine, eicosanoids, leukotrienes, and cytokines) involved in inflammation.

12.2 Pharmacodynamics

Cardiac Electrophysiology

In a placebo-controlled trial (95 patients with allergic rhinitis), there was no evidence of an effect of azelastine hydrochloride nasal spray (2 sprays per nostril twice daily for 56 days) on cardiac repolarization as represented by the corrected QT interval (QTc) of the electrocardiogram. Following multiple dose oral administration of azelastine 4 mg or 8 mg twice daily, the mean change in QTc was 7.2 msec and 3.6 msec, respectively.

Interaction studies investigating the cardiac repolarization effects of concomitantly administered oral azelastine hydrochloride and erythromycin or ketoconazole were conducted. These drugs had no effect on QTc based on analysis of serial electrocardiograms.

12.3 Pharmacokinetics

Absorption

After nasal administration of two sprays per nostril (548 mcg of azelastine hydrochloride and 200 mcg of fluticasone) of DYMISTA, the mean (± standard deviation) peak plasma exposure (Cmax) was 194.5 ± 74.4 pg/mL for azelastine and 10.3 ± 3.9 pg/mL for fluticasone propionate and the mean total exposure (AUC) was 4217 ± 2618 pg/mL*hr for azelastine and 97.7 ± 43.1 pg/mL*hr for fluticasone. The median time to peak exposure (tmax) from a single dose was 0.5 hours for azelastine and 1.0 hours for fluticasone.

Systemic bioavailability of azelastine from DYMISTA following nasal administration was comparable with monotherapy azelastine hydrochloride (Astelin®) nasal spray (i.e., approximately 40%). Systemic bioavailability of fluticasone from DYMISTA following nasal administration was 44-61% higher than monotherapy fluticasone propionate (bioavailability for monotherapy fluticasone nasal spray was less than 2%). Due to the low nasal bioavailability, pharmacokinetic data for fluticasone propionate were obtained via other routes of administration. Studies using oral dosing of radiolabeled fluticasone propionate showed negligible oral bioavailability and high extraction from plasma. The majority of the circulating radioactivity was due to an inactive metabolite.

Distribution

Based on intravenous and oral administration, the steady-state volume of distribution of azelastine hydrochloride is 14.5 L/kg. In vitro studies with human plasma indicate that the plasma protein binding of azelastine hydrochloride and its metabolite, desmethylazelastine, are approximately 88% and 97%, respectively.

Following intravenous administration, the initial disposition phase for fluticasone propionate was rapid and consistent with its high lipid solubility and tissue binding. The volume of distribution averaged 4.2 L/kg.

The percentage of fluticasone propionate bound to human plasma proteins averaged 91% with no obvious concentration relationship. Fluticasone propionate is weakly and reversibly bound to erythrocytes and freely equilibrates between erythrocytes and plasma. Fluticasone propionate is not significantly bound to human transcortin.

Elimination

Following nasal administration of DYMISTA, the elimination half-life of azelastine hydrochloride is approximately 25 hours. Approximately 75% of an oral dose of radiolabeled azelastine hydrochloride was excreted in the feces with less than 10% as unchanged azelastine.

Following intravenous dosing, fluticasone propionate showed polyexponential kinetics and had a terminal elimination half-life of approximately 7.8 hours. Less than 5% of a radiolabeled oral dose was excreted in the urine as metabolites, with the remainder excreted in the feces as parent drug and metabolites.

Metabolism

Azelastine hydrochloride is oxidatively metabolized to the principal active metabolite, desmethylazelastine, by the cytochrome P450 enzyme system. The specific P450 isoforms responsible for the biotransformation of azelastine have not been identified. The total clearance of azelastine is approximately 0.50 L/kg/hr.

For fluticasone propionate, the only circulating metabolite detected in man is the 17β-carboxylic acid derivative, which is formed through the CYP3A4 pathway. This inactive metabolite had less affinity (approximately 1/2,000) than the parent drug for the glucocorticoid receptor of human lung cytosol in vitro and negligible pharmacological activity in animal studies. Other metabolites detected in vitro using cultured human hepatoma cells have not been detected in man. The average total clearance of fluticasone propionate is relatively high (approximately 66 L/hr).

Specific Populations

DYMISTA was not studied in any specific populations, and no gender-specific pharmacokinetic data have been obtained.

Following oral administration of azelastine hydrochloride, pharmacokinetic parameters were not influenced by hepatic impairment, age, or gender. The effect of race has not been evaluated.

Patients with Renal Impairment

Based on oral, single-dose studies of azelastine hydrochloride, renal impairment (creatinine clearance < 50 mL/min) resulted in a 70-75% higher Cmax and AUC compared to healthy subjects. Time to maximum concentration was unchanged.

Drug Interaction Studies

No formal drug interaction studies have been performed with DYMISTA. The drug interactions of the combination are expected to reflect those of the individual components.

Erythromycin

Coadministration of orally administered azelastine (4 mg twice daily) with erythromycin (500 mg three times daily for 7 days) resulted in Cmax of 5.36 ± 2.6 ng/mL and AUC of 49.7 ± 24 ng•h/mL for azelastine, whereas, administration of azelastine alone resulted in Cmax of 5.57 ± 2.7 ng/mL and AUC of 48.4 ± 24 ng•h/mL for azelastine.

In another multiple-dose drug interaction study, coadministration of orally inhaled fluticasone propionate (500 mcg twice daily) and erythromycin (333 mg three times daily) did not affect fluticasone propionate pharmacokinetics.

Cimetidine and Ranitidine

In a multiple-dose, steady-state drug interaction trial in healthy subjects, cimetidine (400 mg twice daily) increased orally administered mean azelastine hydrochloride (4 mg twice daily) concentrations by approximately 65%. Coadministration of orally administered azelastine hydrochloride (4 mg twice daily) with ranitidine hydrochloride (150 mg twice daily) resulted in Cmax of 8.89 ± 3.28 ng/mL and AUC of 88.22 ± 40.43 ng•h/mL for azelastine hydrochloride, whereas, administration of azelastine hydrochloride alone resulted in Cmax of 7.83 ± 4.06 ng/mL and AUC of 80.09 ± 43.55 ng•h/mL for azelastine hydrochloride.

Theophylline

No significant pharmacokinetic interaction was observed with the coadministration of an oral 4 mg dose of azelastine hydrochloride twice daily and theophylline 300 mg or 400 mg twice daily.

Ritonavir

Coadministration of fluticasone propionate and the strong CYP3A4 inhibitor, ritonavir, is not recommended based upon a multiple-dose, crossover drug interaction study in 18 healthy subjects. Fluticasone propionate aqueous nasal spray (200 mcg once daily) was coadministered for 7 days with ritonavir (100 mg twice daily). Plasma fluticasone propionate concentrations following fluticasone propionate aqueous nasal spray alone were undetectable (< 10 pg/mL) in most subjects, and when concentrations were detectable, peak levels (Cmax) averaged 11.9 pg/mL (range, 10.8 to 14.1 pg/mL) and AUC(0-τ) averaged 8.43 pg•hr/mL (range, 4.2 to 18.8 pg•hr/mL). Fluticasone propionate Cmax and AUC(0-τ) increased to 318 pg/mL (range, 110 to 648 pg/mL) and 3,102.6 pg•hr/mL (range, 1,207.1 to 5,662.0 pg•hr/mL), respectively, after coadministration of ritonavir with fluticasone propionate aqueous nasal spray. This significant increase in plasma fluticasone propionate exposure resulted in a significant decrease (86%) in plasma cortisol area under the plasma concentration versus time curve (AUC).

Caution should be exercised when other strong CYP3A4 inhibitors are coadministered with fluticasone propionate. In a drug interaction study, coadministration of orally inhaled fluticasone propionate (1,000 mcg) and ketoconazole (200 mg once daily) resulted in increased fluticasone propionate exposure and reduced plasma cortisol AUC, but had no effect on urinary excretion of cortisol [see Drug Interactions (7.2)].

13 NONCLINICAL TOXICOLOGY

13.1 Carcinogenesis, Mutagenesis, Impairment of Fertility

DYMISTA

No studies of carcinogenicity, mutagenicity, or impairment of fertility were conducted with DYMISTA; however, studies are available for the individual active components, azelastine hydrochloride and fluticasone propionate, as described below.

Azelastine Hydrochloride

Two-year carcinogenicity studies in Crl:CD(SD)BR rats and NMRI mice were conducted to assess the carcinogenic potential of azelastine hydrochloride. No evidence of tumorigenicity was observed in rats at doses up to 30 mg/kg/day (approximately 530 and 240 times the MRHDID for adults and children, respectively, on a mg/m^2 basis). No evidence for tumorigenicity was observed in mice at doses up to 25 mg/kg (approximately 220 and 100 times the MRHDID for adults and children, respectively, on a mg/m^2 basis).

Azelastine hydrochloride showed no genotoxic effects in the Ames test, DNA repair test, mouse lymphoma forward mutation assay, mouse micronucleus test, or chromosomal aberration test in rat bone marrow.

There were no effects on male or female fertility and reproductive performance in male and female rats at oral doses up to 30 mg/kg (approximately 530 times the MRHDID in adults on a mg/m^2 basis). At 68.6 mg/kg (approximately 1200 times the MRHDID on a mg/m^2 basis), the duration of estrous cycles was prolonged and copulatory activity and the number of pregnancies were decreased. The numbers of corpora lutea and implantations were decreased; however, pre-implantation loss was not increased.

Fluticasone Propionate

Fluticasone propionate demonstrated no tumorigenic potential in mice at oral doses up to 1,000 mcg/kg (approximately 25 and 10 times the MRHDID in adults and children, respectively, on a mcg/m^2 basis) for 78 weeks or in rats at inhalation doses up to 57 mcg/kg (approximately 3 and 1 times the MRHDID in adults and children, respectively, on a mcg/m^2 basis) for 104 weeks.

Fluticasone propionate did not induce gene mutation in prokaryotic or eukaryotic cells in vitro. No significant clastogenic effect was seen in cultured human peripheral lymphocytes in vitro or in the mouse micronucleus test.

Fertility and reproductive performance were unaffected in male and female rats at subcutaneous doses up to 50 mcg/kg (approximately 2 times the MRHDID for adults on a mcg/m^2 basis).

14 CLINICAL STUDIES

Adults and Adolescents 12 Years of Age and Older: The efficacy and safety of DYMISTA in adults and adolescents 12 years of age and older with seasonal allergic rhinitis was evaluated in 3 randomized, multicenter, double-blind, placebo-controlled clinical trials in 853 patients. The population of the trials was 12 to 78 years of age (64% female, 36% male; 80% white, 16% black, 2% Asian, 1% other).

Patients were randomized to one of four treatment groups: one spray per nostril twice daily of DYMISTA, azelastine hydrochloride nasal spray, fluticasone propionate nasal spray, and vehicle placebo. The azelastine hydrochloride and fluticasone propionate comparators use the same device and vehicle as DYMISTA and are not commercially marketed. Assessment of efficacy was based on the reflective total nasal symptom score (rTNSS), in addition to the instantaneous total nasal symptom score (iTNSS) and other supportive secondary efficacy variables. TNSS is calculated as the sum of the patients’ scoring of the 4 individual nasal symptoms (rhinorrhea, nasal congestion, sneezing, and nasal itching) on a 0 to 3 categorical severity scale (0 = absent, 1 = mild, 2 = moderate, 3 = severe). Patients were required to record symptom severity daily reflecting over the previous 12 hours (morning, AM, and evening, PM). For the primary efficacy endpoint, the combined AM+PM rTNSS (maximum score of 24) was assessed as a change from baseline for each day and then averaged over a 2-week treatment period. The primary efficacy endpoint was the mean change from baseline in combined AM+PM rTNSS over 2 weeks. The iTNSS was recorded immediately prior to the next dose.

In these trials, DYMISTA demonstrated statistically significant greater decreases in rTNSS as compared to azelastine hydrochloride and to fluticasone propionate, as well as to placebo. The differences between the monotherapies and placebo also were statistically significant. Representative results from one of the trials are shown below (Table 3).

Table 3. Mean Change from Baseline in Reflective Total Nasal Symptom Scores Over 2 Weeks [Sum of AM and PM rTNSS for each day (Maximum Score = 24) and averaged over the 14 day treatment period] in Adults and Children ≥ 12 Years with Seasonal Allergic Rhinitis
 |  | Baseline | Change from Baseline | Difference from DYMISTA Nasal Spray
Treatment; (one spray/nostril twice daily) | N | LS Mean | LS Mean | LS Mean | 95% Cl | P-value
DYMISTA | 207 | 18.3 | -5.6 | -- | -- | --
Azelastine HCl Nasal Spray [Not commercially marketed] | 208 | 18.3 | -4.3 | -1.4 | (-2.2, -0.5) | 0.002
Fluticasone Propionate; Nasal Spray | 207 | 18.2 | -4.7 | -1.0 | (-1.8, -0.2) | 0.022
Placebo | 209 | 18.6 | -2.9 | -2.7 | (-3.5, -1.9) | < 0.001
LS Mean, 95% CI, and p-value are obtained from the repeated-measures analysis of covariance model using observed data.

In these trials, DYMISTA also demonstrated statistically significant, greater decreases in iTNSS as compared to placebo, as did the azelastine hydrochloride and fluticasone propionate comparators. Representative results from one of the trials are shown below (Table 4).

Table 4. Mean Change from Baseline in Instantaneous Total Nasal Symptom Scores Over 2 Weeks [Sum of AM and PM rTNSS for each day (Maximum Score = 24) and averaged over the 14 day treatment period] in Adults and Children ≥ 12 Years with Seasonal Allergic Rhinitis
 |  | Baseline | Change from Baseline | Difference from Placebo
Treatment; (one spray/nostril twice daily) | N | LS Mean | LS Mean | LS Mean | 95% Cl | P-value
DYMISTA | 207 | 17.2 | -5.6 | -- | -- | --
Azelastine HCl Nasal Spray [Not commercially marketed] | 208 | 16.8 | -4.3 | -1.4 | (-2.2, -0.5) | 0.002
Fluticasone Propionate; Nasal Spray | 207 | 16.8 | -4.7 | -1.0 | (-1.8, -0.2) | 0.022
Placebo | 209 | 17.3 | -2.9 | -2.7 | (-3.5, -1.9) | < 0.001
LS Mean, 95% CI, and p-value are obtained from the repeated-measures analysis of covariance model using observed data.

Onset of action, defined as the first timepoint at which DYMISTA was statistically superior to placebo in the mean change from baseline in iTNSS and which was sustained thereafter, was assessed in each of the three trials. Onset of action was observed as early as 30 minutes following the initial dose of DYMISTA.

The subjective impact of seasonal allergic rhinitis on patient’s health-related quality of life was evaluated by the Rhinoconjunctivitis Quality of Life Questionnaire (RQLQ) (28 items in 7 domains (activities, sleep, non-nose/eye symptoms, practical problems, nasal symptoms, eye symptoms, and emotional) evaluated on a 7-point scale where 0 = no impairment and 6 = maximum impairment), which was administered to patients 18 years of age and older. An overall RQLQ score is calculated from the mean of all items in the instrument. A change from baseline of at least 0.5 points is considered a clinically meaningful improvement. In each of these trials, DYMISTA demonstrated a statistically significant greater decrease from baseline in the overall RQLQ than placebo, which ranged from -0.55 (95% CI -0.72, -0.39) to -0.80 (95% CI -1.05, -0.55). In these trials, the treatment differences between DYMISTA and the monotherapies were less than the minimum important difference of 0.5 points.

Pediatric Patients 6-11 Years of Age: The efficacy and safety of DYMISTA was evaluated in one randomized, multi-center, double-blind, placebo-controlled trial in 304 children 6 to 11 years of age with seasonal allergic rhinitis. Patients were randomized 1:1 to receive either one spray per nostril twice daily of DYMISTA or placebo (vehicle control) for 14 days. The design of this trial was similar to that of the adult trials.

The primary efficacy endpoint was the mean change from baseline in combined AM+PM reflective total nasal symptom score (rTNSS) over 2 weeks. DYMISTA was not statistically significantly different than placebo, but the results were numerically supportive (Table 5).

Table 5: Mean Change from Baseline in Reflective Total Nasal Symptom Scores Over 2 Weeks in Children Age 6 to 11 Years
Treatment | Baseline | LS Mean Change from baseline | LS Mean Difference (95% CI) | P-value
DYMISTA N = 152 | 18.4 | -3.7 | -0.8 (-1.8, 0.2) | 0.099
Placebo N = 152 | 18.0 | -2.9
CI = confidence interval
LS Mean, 95% CI, and p-value are obtained from the repeated-measures analysis of covariance model using observed data

16 HOW SUPPLIED/STORAGE AND HANDLING

How Supplied: DYMISTA nasal spray (NDC 0037-0245-23) is supplied as an amber glass bottle fitted with a metered-dose spray pump unit. The spray pump unit consists of a nasal spray pump with a white nasal adapter and clear plastic dust cap. Each bottle contains a net fill weight of 23 g and will deliver 120 metered sprays after priming [see Dosage and Administration (2.2)]. After priming [see Dosage and Administration (2.2)], each spray delivers a suspension volume of 0.137 mL as a fine mist, containing 137 mcg of azelastine hydrochloride and 50 mcg of fluticasone propionate (137 mcg/50 mcg). The correct amount of medication in each spray cannot be assured before the initial priming and after 120 sprays have been used, even though the bottle is not completely empty. The bottle should be discarded after 120 sprays have been used.

DYMISTA should not be used after the expiration date “EXP” printed on the bottle label and carton.

Storage: Store upright with the dust cap in place at controlled room temperature 20°C to 25°C (68°F to 77°F). [See USP Controlled Temperature] Protect from light. Do not store in the freezer or refrigerator.

17 PATIENT COUNSELING INFORMATION

See FDA-approved patient labeling (Patient Information and Instructions for Use)

Somnolence: Somnolence has been reported in some patients (8 of 1,269 patients) taking DYMISTA in controlled clinical trials. Caution patients against engaging in hazardous occupations requiring complete mental alertness and motor coordination such as driving or operating machinery after administration of DYMISTA [see Warnings and Precautions (5.1)].

Concurrent Use of Alcohol and other Central Nervous System Depressants: Advise patients to avoid concurrent use of DYMISTA with alcohol or other central nervous system depressants because additional reductions in alertness and additional impairment of central nervous system performance may occur [see Warnings and Precautions (5.1)].

Local Nasal Effects: Nasal corticosteroids are associated with epistaxis, nasal ulceration, nasal septal perforation, Candida albicans infection and impaired wound healing. Patients who have experienced recent nasal ulcers, nasal surgery, or nasal trauma should not use DYMISTA until healing has occurred [see Warnings and Precautions (5.2)].

Glaucoma and Cataracts: Inform patients that glaucoma and cataracts are associated with nasal and inhaled corticosteroid use. Advise patients to inform his/her health care provider if a change in vision is noted while using DYMISTA [see Warnings and Precautions (5.3)].

Immunosuppression and Risk of Infections: Warn patients who are on immunosuppressant doses of corticosteroids to avoid exposure to chickenpox or measles and, if exposed, to consult their physician without delay. Inform patients of potential worsening of existing tuberculosis, fungal, bacterial, viral or parasitic infections, or ocular herpes simplex [see Warnings and Precautions (5.4)].

Effect on Growth: Corticosteroids may cause a reduction in growth velocity when administered to pediatric patients. Monitor the growth routinely of pediatric patients receiving DYMISTA [see Use in Specific Populations (8.4)].

Priming: Instruct patients to shake the bottle gently before each use and prime the pump before initial use and when DYMISTA has not been used for 14 or more days [see Dosage and Administration (2.2)].

Keep Spray Out of Eyes: Instruct patients to avoid spraying DYMISTA into their eyes.

Potential Drug Interactions: Advise patients that coadministration of DYMISTA and ritonavir is not recommended and to be cautious if DYMISTA is coadministered with ketoconazole [see Drug Interactions (7.2)].

U.S. Patent 8,168,620

Manufactured by:
Cipla Ltd. Indore SEZ, Pithampur, India
M.L. No. 28/2/2010

Manufactured for:
MEDA
Meda Pharmaceuticals Inc.
Canonsburg, PA 15317 U.S.A.

© 2024 Viatris Inc.

DYMISTA and ASTELIN are registered trademarks of Meda Pharmaceuticals Inc., a Viatris Company.

Revised: 12/2024

IN-023A6-05N

PATIENT INFORMATION

DYMISTA (Dy-Mist-A)
(azelastine hydrochloride and fluticasone propionate)
nasal spray

Important: For use in your nose only

What is DYMISTA?

- DYMISTA is a prescription medicine used to treat symptoms of seasonal allergic rhinitis in people 6 years of age and older.
- DYMISTA may help to reduce your nasal symptoms including stuffy nose, runny nose, itching, and sneezing.

It is not known if DYMISTA is safe or effective in children under 4 years of age.

Do not use DYMISTA if you:

- are allergic to azelastine hydrochloride, or fluticasone propionate, or any of the ingredients in DYMISTA. Stop using DYMISTA and get medical help right away if you have symptoms of a serious allergic reaction.
- See the end of the leaflet for a complete list of ingredients in DYMISTA.

Before using DYMISTA tell your healthcare provider about all of your medical conditions, including if you:

- have had recent nasal sores, nasal surgery, or nasal injury.
- have eye or vision problems, such as cataracts or glaucoma (increased pressure in your eye).
- have tuberculosis or any untreated fungal, bacterial, viral infections or eye infections caused by herpes.
- have been near someone who has chickenpox or measles.
- are not feeling well or have any other symptoms that you do not understand.
- are pregnant or plan to become pregnant.
- are breastfeeding or plan to breastfeed. It is not known if DYMISTA passes into your breast milk. Talk to your healthcare provider about the best way to feed your baby while using DYMISTA.

Tell your healthcare provider about all the medicines you take, including prescription and over-the-counter medicines, vitamins, and herbal supplements.

DYMISTA and other medicines may affect each other, causing side effects.

Especially tell your healthcare provider if you take:

- antifungal or anti-HIV medicines

Ask your healthcare provider or pharmacist for a list of these medicines, if you are not sure.

Know the medicines you take. Keep a list of your medicines and show it to your healthcare provider and pharmacist when you get a new medicine.

How should I use DYMISTA?

- Read the Instructions for Use at the end of this leaflet for information about the right way to use DYMISTA.
- An adult should help a young child use DYMISTA.
- DYMISTA is for use in your nose only. Do not spray it into your eyes or mouth. If you spray DYMISTA into your eyes, flush your eyes with large amounts of water for 10 minutes and then call your healthcare provider.
- Use DYMISTA exactly as your healthcare provider tells you to use it. Your healthcare provider will tell you how much DYMISTA to use and when to use it.
- If a child accidentally swallows DYMISTA or you use too much DYMISTA, call your healthcare provider or go to the nearest hospital emergency room right away.

What should I avoid while using DYMISTA?

- DYMISTA can cause sleepiness or drowsiness. Do not drive, operate machinery, or do anything that needs you to be alert until you know how DYMISTA affects you.
- Do not drink alcohol or take any other medicines that may cause you to feel sleepy while using DYMISTA. It can increase your chances of having serious side effects.

What are the possible side effects of DYMISTA?

DYMISTA may cause serious side effects including:

- sleepiness or drowsiness.
- nasal problems. Symptoms of nasal problems may include:
  - crusting in the nose
  - nosebleeds
  - runny nose
  - hole in the cartilage between your nose (nasal septal perforation). A whistling sound when you breathe may be a symptom of nasal septal perforation.
- slow wound healing. You should not use DYMISTA until your nose has healed if you have a sore in your nose, if you have had surgery on your nose, or if your nose has been injured.
- thrush (candida), a fungal infection in your nose and throat. Tell your healthcare provider if you have any redness or white colored patches in your nose or mouth.
- eye problems, such as glaucoma or cataracts. Some people may have eye problems, including glaucoma and cataracts. You should have regular eye exams when using DYMISTA.
- immune system problems and increased risk of infections. DYMISTA may cause problems with the way your immune system protects your body against infection and increase your risk of infection. Avoid contact with people who have contagious diseases such as chickenpox or measles while you use DYMISTA. Symptoms of infection may include:
  - fever
  - aches or pains
  - chills
  - feeling tired
- adrenal insufficiency. Adrenal insufficiency is a condition in which the adrenal glands do not make enough steroid hormones. Symptoms of adrenal insufficiency may include:
  - tiredness
  - weakness
  - nausea
  - vomiting
  - low blood pressure
- slowed or delayed growth in children. A child's growth should be checked regularly while using DYMISTA.

Call your healthcare provider or get medical help right away if you have symptoms of any of the serious side effects listed above.

The most common side effects of DYMISTA Nasal Spray include:

- changes in taste
- nosebleeds
- headache

Tell your healthcare provider if you have any side effect that bothers you or that does not go away. These are not all of the possible side effects of DYMISTA.

Call your doctor for medical advice about side effects. You may report side effects to FDA at 1-800-FDA-1088.

How should I store DYMISTA?

- Store DYMISTA upright with the dust cap in place at room temperature between 68°F to 77°F (20°C to 25°C).
- Do not freeze or refrigerate DYMISTA.
- Protect DYMISTA from light.
- Do not use DYMISTA after the expiration date “EXP” printed on the bottle label and carton.
- Throw away your DYMISTA bottle after using 120 sprays after initial priming. Even though the bottle may not be completely empty, you may not get the correct dose of medicine if you continue to use it.

Keep DYMISTA and all medicines out of reach of children.

General information about the safe and effective use of DYMISTA

Medicines are sometimes prescribed for purposes other than those listed in a Patient Information leaflet. Do not use DYMISTA for a condition for which it was not prescribed. Do not give DYMISTA to other people, even if they have the same symptoms that you have. It may harm them. You can ask your pharmacist or healthcare provider for information about DYMISTA that is written for health professionals.

What are the ingredients in DYMISTA?
Active ingredients: azelastine hydrochloride and fluticasone propionate

Inactive ingredients: benzalkonium chloride, carboxymethylcellulose sodium, edetate disodium, glycerin, microcrystalline cellulose, phenylethyl alcohol, polysorbate 80, and purified water.

For more information, go to www.DYMISTA.com or call Meda Pharmaceuticals Inc. at 1-888-939-6478.

Instructions for Use

DYMISTA (Dy-Mist-A)
(azelastine hydrochloride and fluticasone propionate)
nasal spray

For use in your nose only. Do not spray in your eyes.

Read the Instructions for Use before you start to use DYMISTA and each time you get a refill. There may be new information. This leaflet does not take the place of talking with your healthcare provider about your medical condition or treatment. Before you use DYMISTA, make sure your healthcare provider shows you the right way to use it.

Shake the bottle gently before each use.

Your DYMISTA pump. (See Figure A)

Figure A

Instructions for Using Your DYMISTA Pump.

Before you use DYMISTA for the first time, you will need to shake the bottle gently and prime the pump.

For use in young children: An adult should help a young child use DYMISTA. (See Steps 1 through 12).

Priming your DYMISTA pump
Before you prime the bottle, shake it gently.

Step 1.

Remove the clear plastic dust cap from the spray pump tip of the bottle. (See Figure B)

Figure B

Step 2.

Hold the bottle upright with two fingers on the shoulders of the spray pump unit and put your thumb on the bottom of the bottle. Press upward with your thumb and release for the pumping action.

- Repeat the pumping action until you see a fine mist. You should see a fine mist of the medicine after 6 pumps or less. (See Figure C)
- To get a fine mist of medicine, you must repeat the pumping action fast and use firm pressure against the bottom of the bottle.
- If you see a stream of liquid, the spray will not work right and may cause nasal discomfort.
- If you do not use DYMISTA for 14 or more days, you will need to shake the bottle gently, and prime the pump with 1 spray or until you see a fine mist. If you do not see a fine mist, clean the tip of the spray nozzle. See the cleaning section below.
- Once you see the fine mist of medicine, your DYMISTA pump is ready for use.

Figure C

Using your DYMISTA:

For use in young children: An adult should help a young child use DYMISTA.

Step 3.

Gently blow your nose to clear nostrils. (See Figure D)

Figure D

Step 4.

Shake the bottle gently. Close 1 nostril with a finger. Tilt your head forward slightly. Keep the bottle upright and carefully place the spray pump tip ¼ to ½ inch into your other nostril. (See Figure E)

Figure E

Step 5.

For each spray firmly press the pump 1 time. Keep your head tilted down and at the same time, gently breathe in through your nostril. (See Figure F)

Do not spray directly onto the nasal septum (the wall between your 2 nostrils).

- Repeat Step 5 in your other nostril.
- Do not tilt your head back. This will help to keep the medicine from going into your throat.
- If the medicine goes into your throat you may get a bitter taste in your mouth. This is normal.

Figure F

Step 6.

When you finish using DYMISTA, wipe the spray tip with a clean tissue or cloth. Put the dust cap back on the spray pump tip of the bottle. (See Figure G)

Figure G

Each bottle of DYMISTA contains enough medicine for you to spray medicine from the bottle 120 times. After initial priming, do not use your bottle of DYMISTA after 120 sprays. You may not receive the right amount of medicine. Keep track of the number of sprays you use from your bottle of DYMISTA and throw away the bottle even if it has medicine left in it.

Do not count any sprays used for initially priming the bottle.

Cleaning the Spray Pump Tip:

Your DYMISTA should be cleaned at least 1 time each week. To do this:

Step 7.

Remove the dust cap and then gently pull upward on the spray pump unit to remove it from the bottle. (See Figure H)

Figure H

Step 8.

Wash the spray pump unit and dust cap in warm tap water. (See Figure I)

Figure I

Step 9.

Allow to dry completely. When dry, place the spray pump unit and dust cap back on the bottle. (See Figure J)

Figure J

Step 10.

If the spray pump unit becomes blocked, it can be removed as instructed above in Step 7 and placed in warm water to soak.

Do not try to unblock the spray pump unit by inserting a pin or other sharp object. This will damage the spray pump unit and cause you not to get the right dose of medicine.

Step 11.

After the spray pump unit is unblocked, rinse the applicator and cap with cold water, and allow them to dry as in Step 10 above. When dry, place the spray pump unit back on the bottle and put the dust cap on the spray pump tip.

Step 12.

Reprime the bottle as in Steps 1 and 2 above. Replace the dust cap and your DYMISTA is ready for use.

This Patient Information and Instructions for Use has been approved by the U.S. Food and Drug Administration.

U.S. Patent 8,168,620

Manufactured by:
Cipla Ltd. Indore SEZ, Pithampur, India
M.L. No. 28/2/2010

Manufactured for:
MEDA
Meda Pharmaceuticals Inc.
Canonsburg, PA 15317 U.S.A.

© 2024 Viatris Inc.

DYMISTA is a registered trademark of Meda Pharmaceuticals Inc., a Viatris Company.

Revised: 12/2024

IN-023A6-05N

PRINCIPAL DISPLAY PANEL - 137 mcg/50 mcg per Spray

NDC 0037-0245-23

Dymista®
(azelastine hydrochloride
and
fluticasone propionate)
Nasal Spray
137 mcg / 50 mcg per spray

120 Metered Sprays

FOR NASAL USE ONLY

Rx Only

23 g net fill weight

Shake the bottle gently
before each use.

Each spray delivers 0.137 mL
(137 mcg azelastine
hydrochloride and 50 mcg
fluticasone propionate).

Contents: An aqueous
suspension containing azelastine
hydrochloride, fluticasone
propionate, glycerin,
microcrystalline cellulose and
carboxymethylcellulose sodium,
phenylethyl alcohol (2.5 mg/g),
edetate disodium, benzalkonium
chloride (0.1 mg/g), polysorbate
80 and purified water, pH 6.

Dosage: See enclosed full
Prescribing Information.

Storage:
Store upright, with dust cap
in place, at controlled room
temperature 20°C to 25°C (68°F
to 77°F). Protect from light. Do not
store in the freezer or refrigerator.

Keep away from children.

FOR NASAL USE ONLY

Read PATIENT INSTRUCTIONS FOR USE
for additional information on how to
use the product.

Dosing Instructions

CLEAR YOUR NOSE

Clear your nostrils by gently
blowing your nose.

LOOK AT YOUR TOES

Tilt your head down to keep the
medicine from going into your throat.

SPRAY AND SNIFF GENTLY

Shake the bottle gently before
each use.

Spray a fine mist, once per nostril.

Remember to sniff gently.

Discard after 120 actuations.

For assistance call 1-888-939-6478
www.DYMISTA.com

DYMISTA is a registered trademark of Meda
Pharmaceuticals Inc., a Viatris Company.

Shake the bottle gently
before each use.

Initial Priming: 6 sprays or
until a fine mist appears.

Repriming (only if you have not used
Dymista for 14 or more days): 1 spray
or until a fine mist appears.

FOR NASAL USE ONLY

Manufactured by: Cipla Ltd.,
Indore SEZ, Pithampur, India

M.L. No. 28/2/2010

For: Meda Pharmaceuticals Inc.
Canonsburg, PA 15317 U.S.A.

© 2024 Viatris Inc.

UC-023A6-04N

U.S. Patent 8,168,620